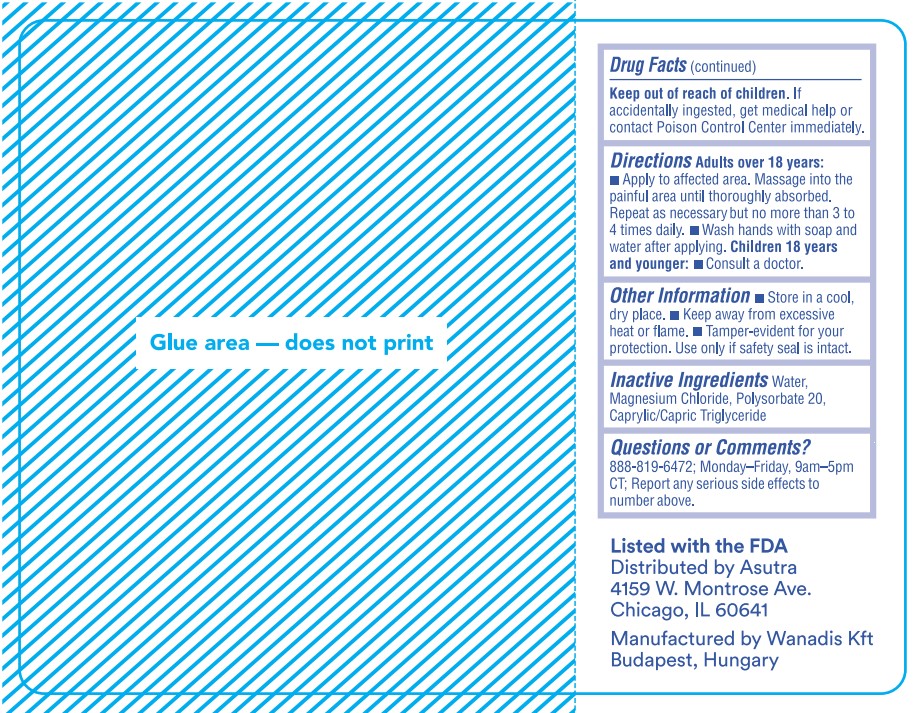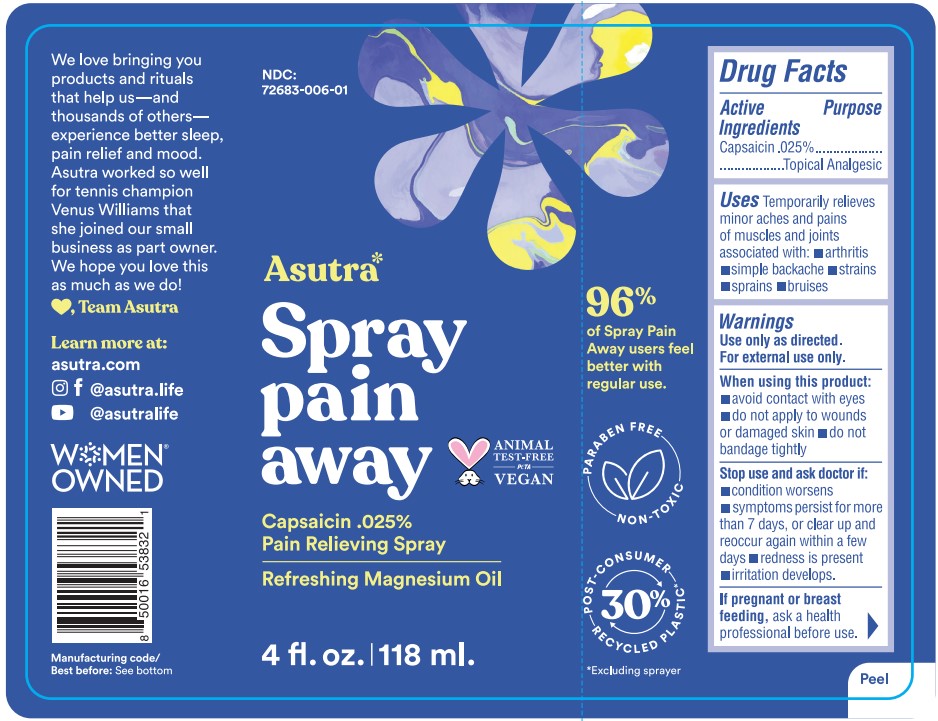 DRUG LABEL: SprayPain Away
NDC: 72683-006 | Form: SPRAY
Manufacturer: Proximity Capital Partners LLC dba Asutra
Category: otc | Type: HUMAN OTC DRUG LABEL
Date: 20250618

ACTIVE INGREDIENTS: CAPSAICIN 0.025 g/100 g
INACTIVE INGREDIENTS: WATER; MAGNESIUM CHLORIDE; POLYSORBATE 20; MEDIUM-CHAIN TRIGLYCERIDES

Spray Pain Away (Asutra)

Active ingredients

Capsaicin .025%

Purpose

Capsaicin .025%.............Topical Analgesic

Uses

Temporarily relieves minor aches and pains of muscles and joints associated with:

- arthritis
- simple backache
- strains
- sprains
- bruises

Warnings

Use only as directed. For external use only.

When using this product:

- avoid contact with eyes
- do not apply to wounds or damaged skin
- do not bandage tightly

Stop use and ask doctor if:

- condition worsens
- symptoms persist for more than 7 days, or clear up and reoccur again within a few days
- redness is present
- irritation develops.

PREGNANCY OR BREAST FEEDING

If pregnant or breast feeding,ask a health professional before use.

Keep out of reach of children.If accidentally ingested, get medical help or contact a Poison Control Center immediately.

Directions

Adults over 18 years:

- Apply to affected area. Massage into the painful area until thoroughly absorbed. Repeat as necessary but no more than 3 to 4 times daily.
- Wash hands with soap and water after applying.

Children 18 years and younger:

- Consult a doctor.

Other information

- Store in a cool, dry place.
- Keep away from excessive heat or flame.
- Tamper-evident for your protection. Use only if safety seal is intact.

Inactive ingredients

Water, Magnesium Chloride, Polysorbate 20, Caprylic/Capric Triglyceride

Questions or Comments?

888-819-6472; Monday-Friday, 9am-5pm CT; Report any serious side effects to number above.

PACKAGE LABEL

NDC:

72683-006-01

Asutra*

Spray

pain

away

Capsaicin .025%

Pain Relieving Spray

Refreshing Magnesium Oil

4 fl. oz. | 118 ml.

Paraben Free

Animal Test-Free PETA Vegan